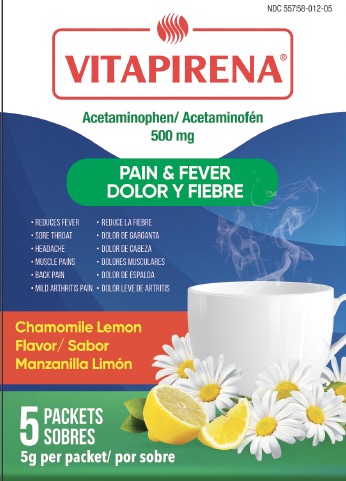 DRUG LABEL: Vitapirena
NDC: 55758-012 | Form: GRANULE, FOR SOLUTION
Manufacturer: Pharmadel LLC
Category: otc | Type: HUMAN OTC DRUG LABEL
Date: 20251222

ACTIVE INGREDIENTS: ACETAMINOPHEN 500 mg/1 1
INACTIVE INGREDIENTS: ANHYDROUS CITRIC ACID; SODIUM BICARBONATE; POVIDONE K30; WATER; FRUCTOSE; SUCRALOSE; SILICON DIOXIDE

Vitapirina Acetaminophen (V)

Active ingredient & Purposes

Active ingredient (in each packet) | Purposes
Acetaminophen 500 mg | Pain reliever/ fever reducer

Uses

For the temporary relief of minor aches and pains associated with

- sore throat
- headache
- the common cold/ flu
- muscular aches
- backache
- minor pain from arthritis
- and to reduce fever

Warnings

Liver warning: This product contains acetaminophen. Severe liver damage may occur if:

- adult takes more than 8 packets in 24 hours, which is the maximum daily amount for this

product

- child takes more than 5 packets in 24 hours
- with other drugs containing acetaminophen
- adult has 3 or more alcoholic drinks everyday while using this product

Sore throat warning: If sore throat is severe, persists for more than 2 days, is accompanied or followed by fever, headache, rash, nausea, or vomiting, consult a doctor promptly.

Do not use

- with any other drug containing acetaminophen (prescription or nonprescription). If you are not sure whether a drug contains acetaminophen, ask a doctor or pharmacist.
- if allergic to acetaminophen or any other of the inactive ingredients in this product

Ask a doctor before use if the user

- has liver disease
- is a child with pain from arthritis

Ask a doctor or pharmacist before use if the user is

- taking the blood thinning drug warfarin

Stop use and ask a doctor if

- adult’s pain gets worse or lasts more than 10 days
- child’s pain gets worse or lasts more than 5 days
- fever gets worse or lasts more than 3 days
- redness or swelling is present
- any new symptoms appear

If pregnant or breastfeeding,

ask a health professional before use.

Keep out of reach of children.

In case of an accidental overdose, get medical help or contact a Poison Control Center right away. Prompt medical attention is critical for adults as well as for children even if you do not notice any signs or symptoms.

Directions

- do not take more than directed

Age | Dose
adults and children 12 years of age and over | take one (1) packet, every 4 hours. Do not exceed; adults 8 packets or children 5 packets in 24 hours
children under 12 years of age | do not use

Other information

- each 5g packet contains: 1 78 mg sodium
- store at room temprature 77-86° F (25-30° C)

Inactive ingredients

chamomile lemon flavor, citric acid monohydrate, fructose, povidone k30, silicon dioxide, sodium bicarbonate, sucralose, water

Questions?

+1-866--359-3478 (M-F) 9 AM - 5 PM EST or www.pharmadel.com

Distributed by:

PHARMADEL LLC.

New Castle, DE 19720